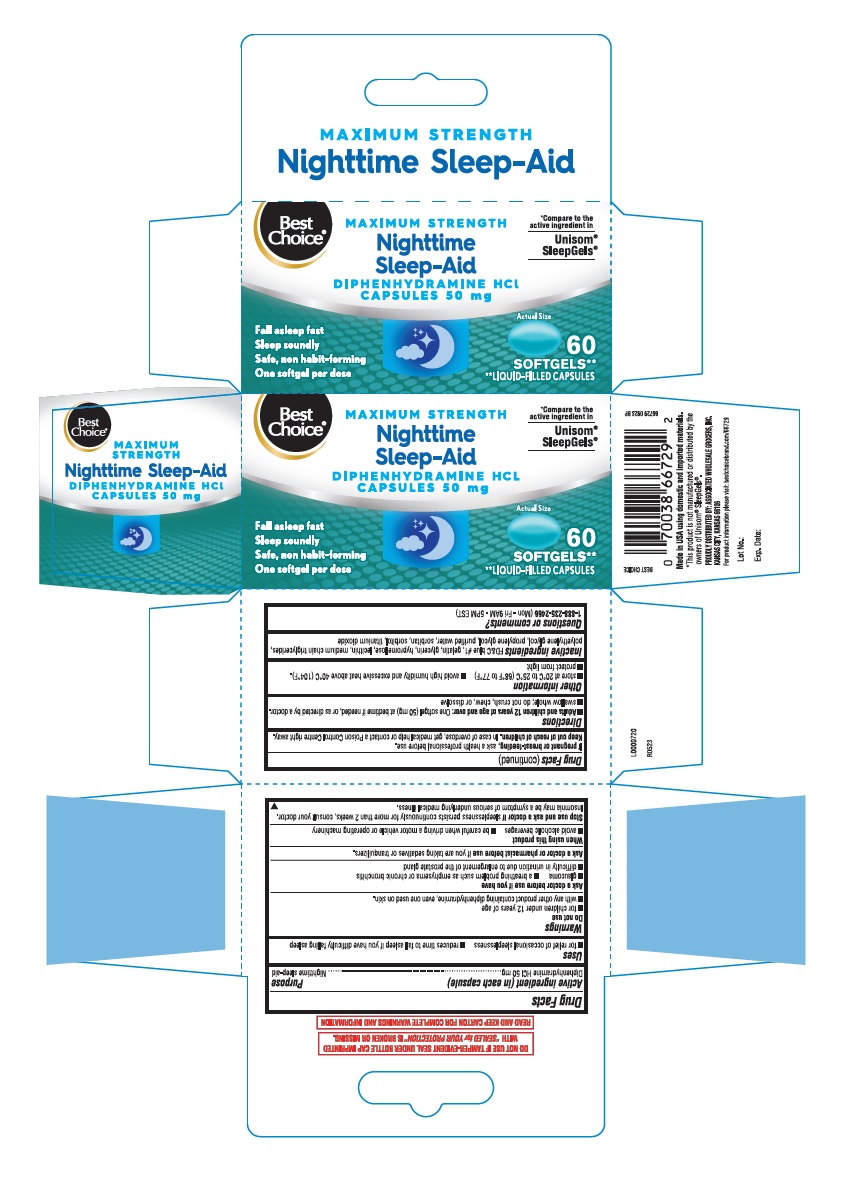 DRUG LABEL: Nighttime Sleep-Aid
NDC: 63941-683 | Form: CAPSULE, LIQUID FILLED
Manufacturer: VALU MERCHANDISERS COMPANY
Category: otc | Type: HUMAN OTC DRUG LABEL
Date: 20231012

ACTIVE INGREDIENTS: DIPHENHYDRAMINE HYDROCHLORIDE 50 mg/1 1
INACTIVE INGREDIENTS: SORBITAN; FD&C BLUE NO. 1; GELATIN; HYPROMELLOSE, UNSPECIFIED; POLYETHYLENE GLYCOL, UNSPECIFIED; LECITHIN, SOYBEAN; WATER; GLYCERIN; MEDIUM-CHAIN TRIGLYCERIDES; PROPYLENE GLYCOL; SORBITOL; TITANIUM DIOXIDE

Diphenhydramine HCl 50mg

Active ingredient (in each capsule)

Diphenhydramine HCl 50 mg

Purpose

Nighttime sleep-aid

Uses

- For relief of occasional sleeplessness
- reduces time to fall asleep if you have difficulty falling asleep

Warnings

Do not use

- for children under 12 years of age
- with any product containing diphenhydramine, even one used on skin.

Ask a doctor before use if you have

- glaucoma
- a breathing problem such as emphysema or chronic bronchitis
- difficulty in urination due to enlargement of the prostate gland

When using this product

- avoid alcoholic beverages
- be careful when driving a motor vehicle or operating machinery

Stop use and ask a doctor if

sleeplessness persists continuosly for more than 2 weeks, consult your doctor.

Insomnia may be a symptom of serious underlying medical illness.

If pregnant or breast- feeding,

ask a health professional before use.

Keep out of reach of children.

In case of overdose, get medical help or contact a Poison Control Centre right away.

Directions

- Adults and children 12 years of age and over: One softgel (50 mg) at bedtime if needed, or as directed by a doctor.
- swallow whole; do not crush, chew, or dissolve

Other information

- store at 20oC to 25oC (68oF to 77oF)
- avoid high humidity and excessive heat above 40oC (104oF).
- protect from light

Inactive ingredients

FD&C blue #1, gelatin, glycerin, hypromellose, lecithin, medium chain truglycerides, polyethylene glycol, purified water, sorbitan, sorbitol, titanium dioxide

Questions or comments?

1-888-235-2466 (Mon-Fri 9AM-5PM EST)

DO NOT USE IF TAMPER-EVIDENT SEAL UNDER BOTTLE CAP IMPRINTED WITH “SEALED for YOUR PROTECTION” IS BROKEN OR MISSING.

READ AND KEEP CARTON FOR COMPLETE WARNINGS AND INFORMATION

Made in USA using domestic and imported materials.

*This product is not manufacturerd or distributed by the owners of Unisom® SleepGels®.

PROUDLY DISTRIBUTED BY: ASSOCIATED WHOLESALE GROCERS, INC.

KANSAS CITY, KANSAS 66106

For product information please visit: bestchoicebrand.com/66729

R0523

L0000720

60's carton

Best

Choice®

*Compare to the

active ingredient in

Unisom®

SleepGels®

MAXIMUM STRENGTH

Nighttime

Sleep-Aid

DIPHENHYDRAMINE HCL

CAPSULES 50 mg

Fall asleep fast

Sleep soundly

Safe, non habit-forming

One softgel per dose

60

SOFTGELS**

**LIQUID-FILLED CAPSULES